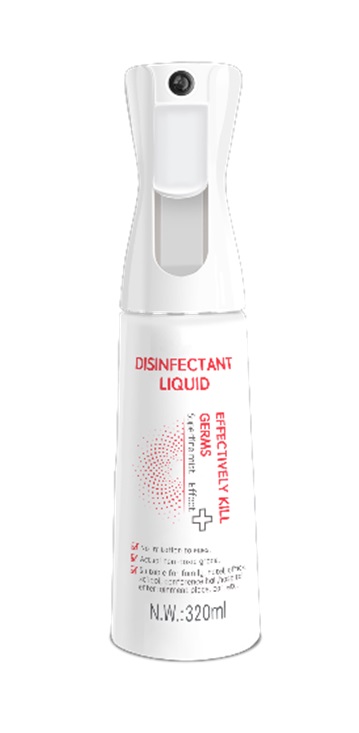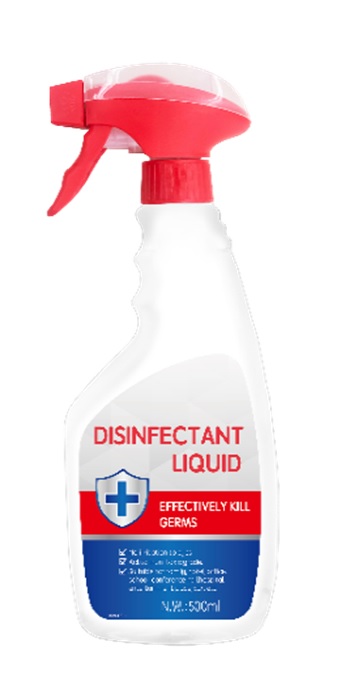 DRUG LABEL: Disinfectant
NDC: 77260-301 | Form: SPRAY
Manufacturer: Shanghai Hutchison Whitecat Co., Ltd.
Category: otc | Type: HUMAN OTC DRUG LABEL
Date: 20200504

ACTIVE INGREDIENTS: BENZALKONIUM CHLORIDE 0.5 g/100 mL
INACTIVE INGREDIENTS: ALCOHOL; LAURETH-4; WATER

Disinfectant

Disinfectant

Active Ingredient(s)

BENZALKONIUM CHLORIDE 0.5g/100mL. Purpose: Antiseptic

Purpose

Antiseptic, Disinfectant

Use

Spray on human skin or surface to disinfect

Warnings

For external use only. Flammable. Keep away from heat or flame

Do not use

- in children less than 2 months of age
- on open skin wounds

When using this product keep out of eyes, ears, and mouth. In case of contact with eyes, rinse eyes thoroughly with water.
Stop use and ask a doctor if irritation or rash occurs. These may be signs of a serious condition.
Keep out of reach of children. If swallowed, get medical help or contact a Poison Control Center right away.

Stop use and ask a doctor if irritation or rash occurs. These may be signs of a serious condition.

Keep out of reach of children. If swallowed, get medical help or contact a Poison Control Center right away.

Directions

- Spray on human skin or surface to disinfect
- Supervise children under 6 years of age when using this product to avoid swallowing.

Other information

- Store between 15-30C (59-86F)
- Avoid freezing and excessive heat above 40C (104F)

Inactive ingredients

WATER
ALCOHOL
BRIJ 35